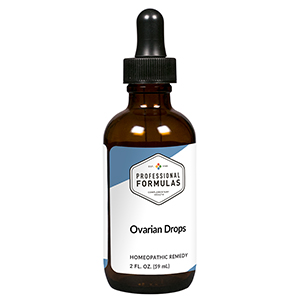 DRUG LABEL: Ovarian Drops
NDC: 63083-5017 | Form: LIQUID
Manufacturer: Professional Complementary Health Formulas
Category: homeopathic | Type: HUMAN OTC DRUG LABEL
Date: 20190815

ACTIVE INGREDIENTS: VIBURNUM OPULUS BARK 2 [hp_X]/59 mL; CHASTE TREE FRUIT 3 [hp_X]/59 mL; ALETRIS FARINOSA ROOT 4 [hp_X]/59 mL; AMARYLLIS BELLADONNA WHOLE 4 [hp_X]/59 mL; DIOSCOREA VILLOSA TUBER 4 [hp_X]/59 mL; APIS MELLIFERA 5 [hp_X]/59 mL; BLACK COHOSH 6 [hp_X]/59 mL; BOS TAURUS OVARY 6 [hp_X]/59 mL; PACKERA AUREA WHOLE 6 [hp_X]/59 mL; SUS SCROFA UTERUS 6 [hp_X]/59 mL; GELSEMIUM SEMPERVIRENS ROOT 8 [hp_X]/59 mL; MAGNESIUM PHOSPHATE, DIBASIC TRIHYDRATE 10 [hp_X]/59 mL
INACTIVE INGREDIENTS: ALCOHOL; WATER

HOD

ACTIVE INGREDIENTS

Viburnum opulus 2X
Agnus castus 3X
Aletris farinosa 4X
Belladonna 4X
Dioscorea villosa 4X
Apis mellifica 5X
Cimicifuga racemosa 6X
Ovary 6X
Senecio aureus 6X
Uterus 6X
Gelsemium sempervirens 8X
Magnesia phosphorica 10X

QUESTIONS

Professional Formulas

PO Box 2034 Lake Oswego, OR 97035

INDICATIONS

For the temporary relief of hot flashes, vaginal dryness, decreased sexual desire, back or abdominal pain or cramping, irritability, or poor concentration.*

PURPOSE

*Claims based on traditional homeopathic practice, not accepted medical evidence. Not FDA evaluated.

WARNINGS

In case of overdose, get medical help or contact a poison control center right away.

Keep out of the reach of children.

PREGNANCY OR BREAST FEEDING

If pregnant or breastfeeding, ask a healthcare professional before use.

DIRECTIONS

Place drops under tongue 30 minutes before/after meals. Adults and children 12 years and over: Take 10 drops up to 3 times per day. Consult a physician for use in children under 12 years of age.

OTHER INFORMATION

Tamper resistant. If seal is broken, do not use. After opening, close container tightly and store at room temperature away from heat.

INACTIVE INGREDIENTS

20% ethanol, purified water.

LABEL

Est 1985

Professional Formulas

Complementary Health

Ovarian Drops

Homeopathic Remedy

2 FL. OZ. (59 mL)